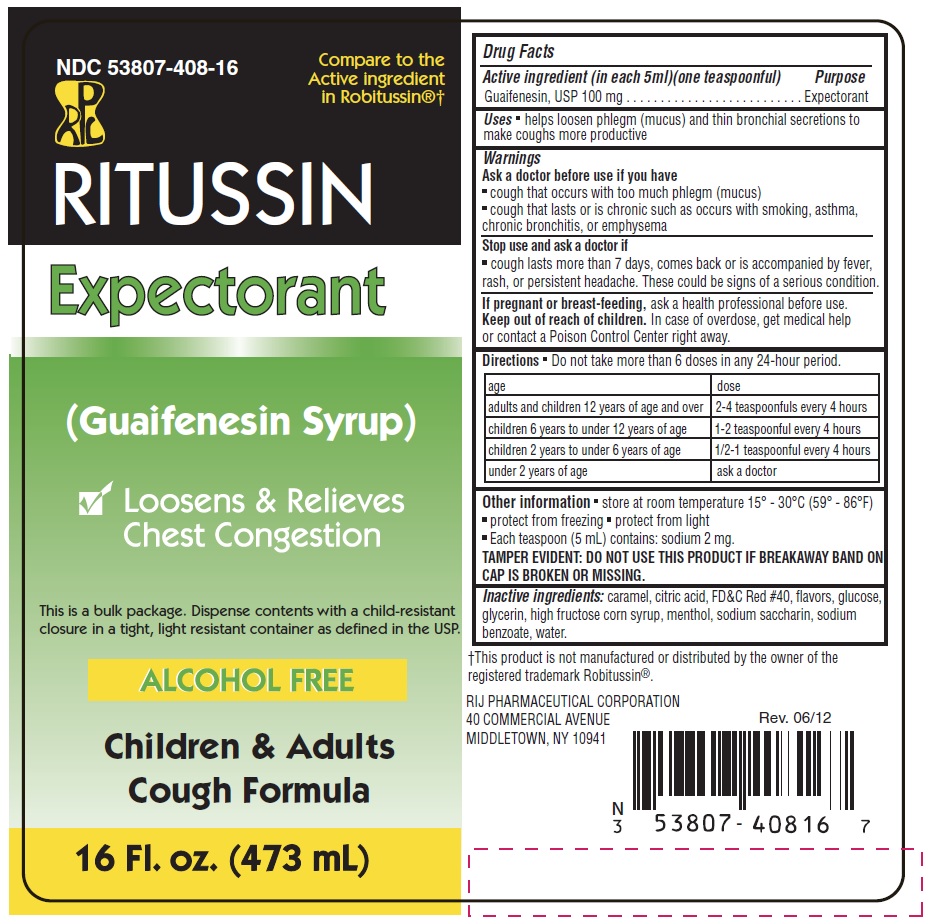 DRUG LABEL: Ritussin Expectorant
NDC: 53807-408 | Form: LIQUID
Manufacturer: Rij Pharmaceutical Corporation
Category: otc | Type: HUMAN OTC DRUG LABEL
Date: 20180430

ACTIVE INGREDIENTS: GUAIFENESIN 100 mg/5 mL
INACTIVE INGREDIENTS: ANHYDROUS CITRIC ACID; CARAMEL; DEXTROSE; FD&C RED NO. 40; HIGH FRUCTOSE CORN SYRUP; MENTHOL; SACCHARIN SODIUM; SODIUM BENZOATE; WATER; GLYCERIN

Drug Facts

Active ingredient (in each 5 mL)(one teaspoonful)

Guaifenesin, USP 100 mg

Purpose

Expectorant

Use

helps loosen phlegm (mucus) and thin bronchial secretions to make coughs more productive

Warnings

Ask a doctor before use if you have

- cough that occurs with too much phlegm (mucus)
- cough that lasts or is chronic such as occurs with smoking, asthma, chronic bronchitis, or emphysema

Stop use and ask a doctor if cough lasts more than 7 days, comes back, or is accompanied by fever, rash, or persistent headache. These could be signs of a serious condition.

PREGNANCY OR BREAST FEEDING

If pregnant or breast-feeding, ask a health professional before use.

Keep out of reach of children. In case of overdose, get medical help or contact a Poison Control Center right away.

Directions

- do not take more than 6 doses in any 24-hour period

age | dose
adults and children 12 years of age and over | 2-4 teaspoons every 4 hours
children 6 years to under 12 years of age | 1-2 teaspoonful every 4 hours
children 2 years to under 6 years of age | 1/2-1 teaspoonful every 4 hours
children under 2 years of age | ask a doctor

Other information

- store at room temperature 15º - 30ºC (59º - 86ºF)
- protect from freezing.
- protect from light.
- Each teaspoon (5 mL) contains: sodium 2 mg.
- TAMPER EVIDENT: DO NOT USE THIS PRODUCT IF BREAKAWAY BAND ON CAP IS BROKEN OR MISSING

Inactive ingredients

caramel, citric acid, FD&C Red #40, , flavors, glucose, glycerin, high fructose corn syrup, menthol, propylene glycol, sodium saccharin, sodium benzoate, water